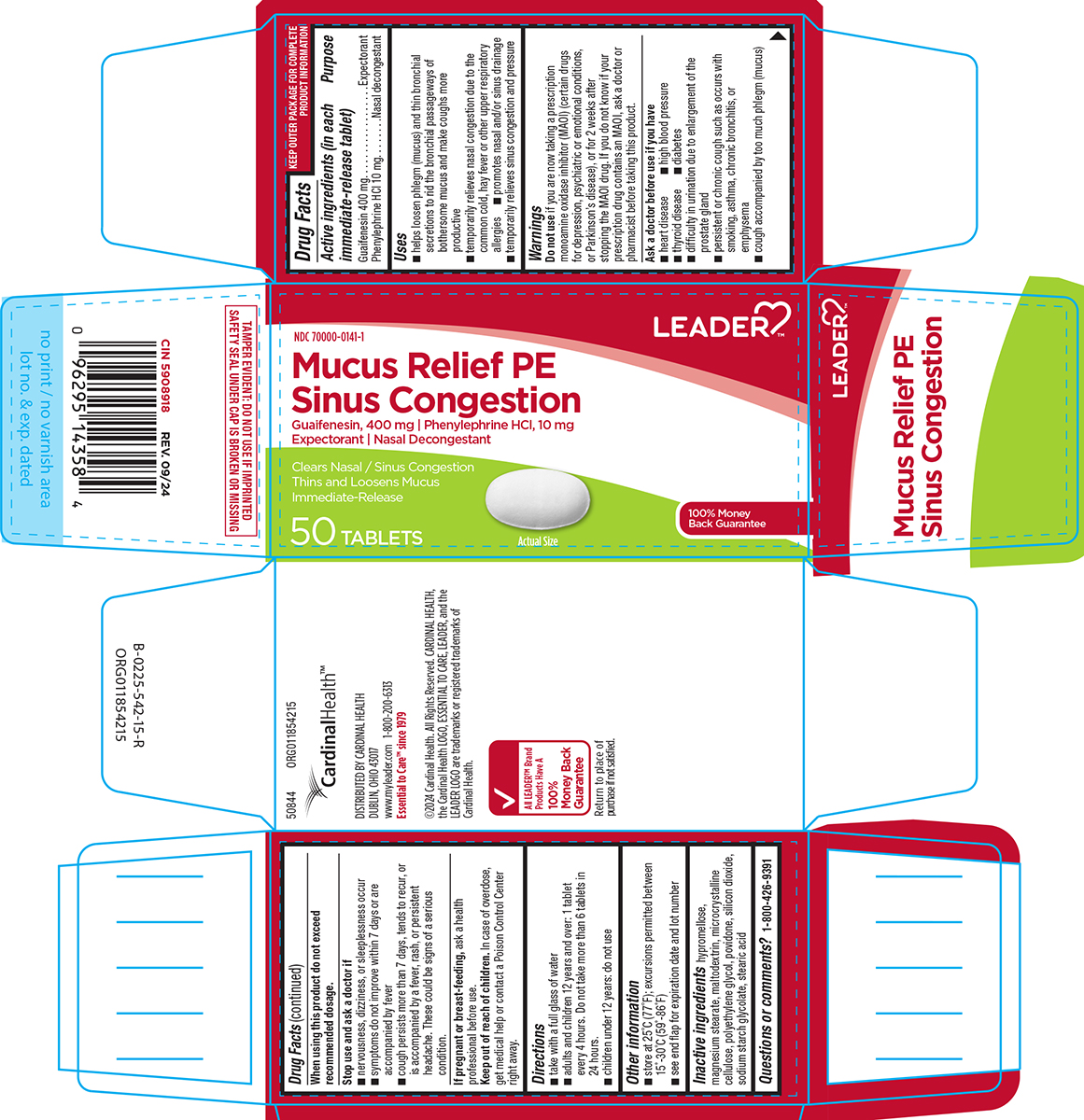 DRUG LABEL: Mucus Relief PE Sinus Congestion
NDC: 70000-0141 | Form: TABLET, FILM COATED
Manufacturer: Cardinal Health 110, LLC. DBA Leader
Category: otc | Type: HUMAN OTC DRUG LABEL
Date: 20251009

ACTIVE INGREDIENTS: GUAIFENESIN 400 mg/1 1; PHENYLEPHRINE HYDROCHLORIDE 10 mg/1 1
INACTIVE INGREDIENTS: HYPROMELLOSE, UNSPECIFIED; MAGNESIUM STEARATE; MALTODEXTRIN; MICROCRYSTALLINE CELLULOSE; POLYETHYLENE GLYCOL, UNSPECIFIED; POVIDONE, UNSPECIFIED; SILICON DIOXIDE; SODIUM STARCH GLYCOLATE TYPE A POTATO; STEARIC ACID

Leader 44-542

Active ingredients (in each immediate-release tablet)

Guaifenesin 400 mg
Phenylephrine HCl 10 mg

Purpose

Expectorant
Nasal decongestant

Uses

- helps loosen phlegm (mucus) and thin bronchial secretions to rid the bronchial passageways of bothersome mucus and make coughs more productive
- temporarily relieves nasal congestion due to the common cold, hay fever or other upper respiratory allergies
- promotes nasal and/or sinus drainage
- temporarily relieves sinus congestion and pressure

Warnings

Do not use

if you are now taking a prescription monoamine oxidase inhibitor (MAOI) (certain drugs for depression, psychiatric or emotional conditions, or Parkinson's disease), or for 2 weeks after stopping the MAOI drug. If you do not know if your prescription drug contains an MAOI, ask a doctor or pharmacist before taking this product.

Ask a doctor before use if you have

- heart disease
- high blood pressure
- thyroid disease
- diabetes
- difficulty in urination due to enlargement of the prostate gland
- cough accompanied by too much phlegm (mucus)
- persistent or chronic cough such as occurs with smoking, asthma, chronic bronchitis, or emphysema

When using this product

do not exceed recommended dosage.

Stop use and ask a doctor if

- nervousness, dizziness, or sleeplessness occur
- symptoms do not improve within 7 days or are accompanied by fever
- cough persists more than 7 days, tends to recur, or is accompanied by a fever, rash, or persistent headache. These could be signs of a serious condition.

If pregnant or breast-feeding,

ask a health professional before use.

Keep out of reach of children.

In case of overdose, get medical help or contact a Poison Control Center right away.

Directions

- take with a full glass of water
- adults and children 12 years and over: 1 tablet every 4 hours. Do not take more than 6 tablets in 24 hours.
- children under 12 years: do not use

Other information

- store at 25°C (77°F); excursions permitted between 15°-30°C (59°-86°F)
- see end flap for expiration date and lot number

Inactive ingredients

hypromellose, magnesium stearate, maltodextrin, microcrystalline cellulose, polyethylene glycol, povidone, silicon dioxide, sodium starch glycolate, stearic acid

Questions or comments?

1-800-426-9391

Principal Display Panel

NDC 70000-0141-1

LEADER™

Mucus Relief PE
Sinus Congestion

Guaifenesin, 400 mg | Phenylephrine HCl, 10 mg
Expectorant | Nasal Decongestant

Relieves Nasal / Sinus Congestion
Thins and Loosens Mucus
Alleviates Chest Congestion

Immediate-Release
50 TABLETS

Actual Size

100% Money Back Guarantee

TAMPER EVIDENT: DO NOT USE IF IMPRINTED SAFETY SEAL UNDER CAP IS BROKEN OR MISSING

CardinalHealth™

DISTRIBUTED BY
CARDINAL HEALTH
DUBLIN, OHIO 43017
www.myleader.com
1-800-200-6313
Essential to Care™ since 1979

©2024 Cardinal Health. All Rights Reserved. CARDINAL HEALTH,
the Cardinal Health LOGO, ESSENTIAL TO CARE, LEADER, and the
LEADER LOGO are trademarks or registered trademarks of
Cardinal Health.

ALL LEADER™ Brand Products Have A
100% Money Back Guarantee
Return to place of purchase if not satisfied.

50844 ORG011854215

Leader 44-542